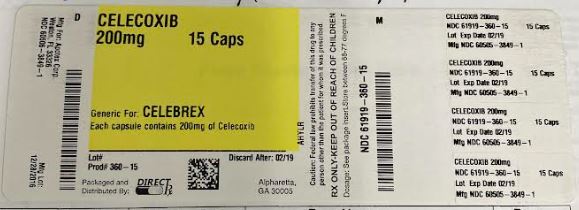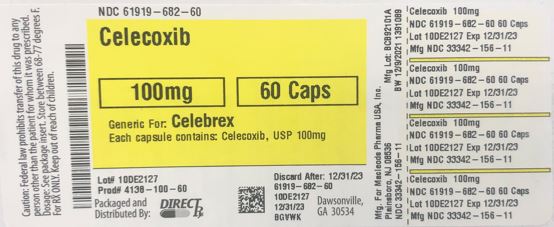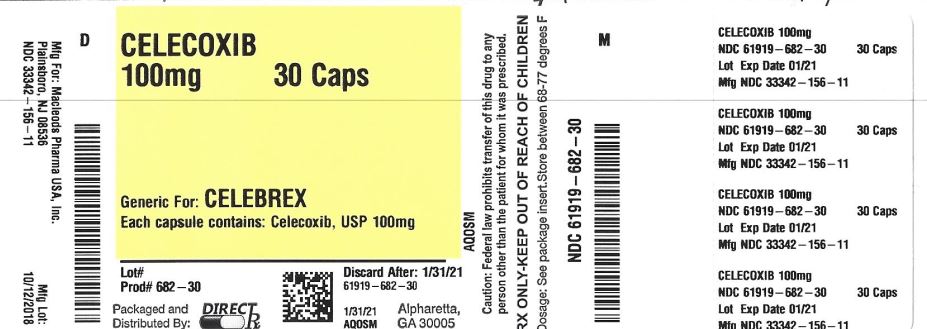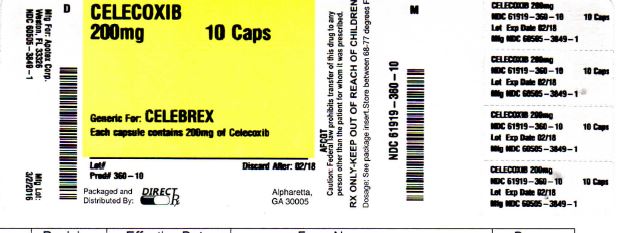 DRUG LABEL: CELECOXIB
NDC: 61919-682 | Form: CAPSULE
Manufacturer: Direct_Rx
Category: prescription | Type: HUMAN PRESCRIPTION DRUG LABEL
Date: 20230418

ACTIVE INGREDIENTS: CELECOXIB 100 mg/1 1
INACTIVE INGREDIENTS: POVIDONE; SODIUM LAURYL SULFATE; HYDROXYPROPYL CELLULOSE (1600000 WAMW); TITANIUM DIOXIDE; GELATIN; FD&C BLUE NO. 2; LACTOSE MONOHYDRATE; MAGNESIUM STEARATE; CROSPOVIDONE (15 MPA.S AT 5%); PROPYLENE GLYCOL

CELECOXIB

Medication Guide for Nonsteroidal Anti-inflammatory Drugs (NSAIDs)
What is the most important information I should know about medicines called Nonsteroidal Anti-inflammatory Drugs (NSAIDs)?
NSAIDs can cause serious side effects, including:

• Increased risk of a heart attack or stroke that can lead to death. This risk may happen early in treatment and may increase:

o with increasing doses of NSAIDs
o with longer use of NSAIDs
Do not take NSAIDs right before or after a heart surgery called a “coronary artery bypass graft (CABG)."

Avoid taking NSAIDs after a recent heart attack, unless your healthcare provider tells you to. You may have an increased risk of another heart attack if you take NSAIDs after a recent heart attack.

• Increased risk of bleeding, ulcers, and tears (perforation) of the esophagus (tube leading from the mouth to the stomach), stomach and intestines:

o anytime during use
o without warning symptoms
o that may cause death
The risk of getting an ulcer or bleeding increases with:

o past history of stomach ulcers, or stomach or intestinal bleeding with use of NSAIDs
o taking medicines called “corticosteroids”, “anticoagulants”, “SSRIs” or “SNRIs”
o increasing doses of NSAIDs o older age
o longer use of NSAIDs o poor health
o smoking o advanced liver disease
o drinking alcohol o bleeding problems

NSAIDs should only be used:

o exactly as prescribed
o at the lowest dose possible for your treatment
o for the shortest time needed

What are NSAIDs?

NSAIDs are used to treat pain and redness, swelling, and heat (inflammation) from medical conditions such as different types of arthritis, menstrual cramps, and other types of short-term pain.

Who should not take NSAIDs?

Do not take NSAIDs:

• if you have had an asthma attack, hives, or other allergic reaction with aspirin or any other NSAIDs.
• right before or after heart bypass surgery.
Before taking NSAIDS, tell your healthcare provider about all of your medical conditions, including if you:

• have liver or kidney problems
• have high blood pressure
• have asthma
• are pregnant or plan to become pregnant. Talk to your healthcare provider if you are considering taking NSAIDs during pregnancy. You should not take NSAIDs after 29 weeks of pregnancy
• are breastfeeding or plan to breast feed.
Tell your healthcare provider about all of the medicines you take, including prescription or over-the-counter medicines, vitamins or herbal supplements. NSAIDs and some other medicines can interact with each other and cause serious side effects. Do not start taking any new medicine without talking to your healthcare provider first.

What are the possible side effects of NSAIDs?

NSAIDs can cause serious side effects, including:

See “What is the most important information I should know about medicines called Nonsteroidal Anti-inflammatory Drugs (NSAIDs)?

• new or worse high blood pressure
• heart failure
• liver problems including liver failure
• kidney problems including kidney failure
• low red blood cells (anemia)
• life-threatening skin reactions
• life-threatening allergic reactions
• Other side effects of NSAIDs include: stomach pain, constipation, diarrhea, gas, heartburn, nausea, vomiting, and dizziness.

Get emergency help right away if you get any of the following symptoms:

• shortness of breath or trouble breathing • slurred speech
• chest pain • swelling of the face or throat
• weakness in one part or side of your body

Stop taking your NSAID and call your healthcare provider right away if you get any of the following symptoms:

• nausea • vomit blood
• more tired or weaker than usual • there is blood in your bowel movement or it is black and sticky like tar
• diarrhea • unusual weight gain
• itching • skin rash or blisters with fever
• your skin or eyes look yellow • swelling of the arms, legs, hands and feet
• indigestion or stomach pain
• flu-like symptoms

If you take too much of your NSAID, call your healthcare provider or get medical help right away.

These are not all the possible side effects of NSAIDs. For more information, ask your healthcare provider or pharmacist about NSAIDs. Call your doctor for medical advice about side effects. You may report side effects to FDA at 1-800-FDA-1088.

Other information about NSAIDs

• Aspirin is an NSAID but it does not increase the chance of a heart attack. Aspirin can cause bleeding in the brain, stomach, and intestines. Aspirin can also cause ulcers in the stomach and intestines.
• Some NSAIDs are sold in lower doses without a prescription (over-the counter). Talk to your healthcare provider before using over-the-counter NSAIDs for more than 10 days.

General information about the safe and effective use of NSAIDs

Medicines are sometimes prescribed for purposes other than those listed in a Medication Guide. Do not use NSAIDs for a condition for which it was not prescribed. Do not give NSAIDs to other people, even if they have the same symptoms that you have. It may harm them. If you would like more information about NSAIDs, talk with your healthcare provider. You can ask your pharmacist or healthcare provider for information about NSAIDs that is written for health professionals.

For more information, call at 1-888-943-3210.

This Medication Guide has been approved by the U.S. Food and Drug Administration.
Manufactured for :
Macleods Pharma USA, Inc.
Plainsboro, NJ 08536

Manufactured by :
Macleods Pharmaceuticals Ltd.
Baddi, Himachal Pradesh, INDIA

Revision Date: May 2016
PM02159404

PATIENT COUNSELING INFORMATION

Advise the patient to read the FDA-approved patient labeling (Medication Guide) that accompanies each prescription dispensed. Inform patients, families, or their caregivers of the following information before initiating therapy with celecoxib capsules and periodically during the course of ongoing therapy.

Cardiovascular Thrombotic Events
Advise patients to be alert for the symptoms of cardiovascular thrombotic events, including chest pain, shortness of breath, weakness, or slurring of speech, and to report any of these symptoms to their health care provider immediately [see Warnings and Precautions (5.1)].

Gastrointestinal Bleeding, Ulceration, and Perforation
Advise patients to report symptoms of ulcerations and bleeding, including epigastric pain, dyspepsia, melena, and hematemesis to their health care provider. In the setting of concomitant use of low-dose aspirin for cardiac prophylaxis, inform patients of the increased risk for and the signs and symptoms of GI bleeding [see Warnings and Precautions (5.2)].

Hepatotoxicity
Inform patients of the warning signs and symptoms of hepatotoxicity (e.g., nausea, fatigue, lethargy, pruritus, diarrhea jaundice, right upper quadrant tenderness, and “flu-like” symptoms). If these occur, instruct patients to stop celecoxib capsules and seek immediate medical therapy [see Warnings and Precautions (5.3), Use in Specific Populations (8.6)].

Heart Failure and Edema
Advise patients to be alert for the symptoms of congestive heart failure including shortness of breath, unexplained weight gain, or edema and to contact their healthcare provider if such symptoms occur [see Warnings and Precautions (5.5)].

Anaphylactic Reactions
Inform patients of the signs of an anaphylactic reaction (e.g., difficulty breathing, swelling of the face or throat). Instruct patients to seek immediate emergency help if these occur [see Contraindications (4) and Warnings and Precautions (5.7)].

Serious Skin Reactions
Advise patients to stop celecoxib capsules immediately if they develop any type of rash and to contact their healthcare provider as soon as possible [see Warnings and Precautions (5.9)].

Female Fertility
Advise females of reproductive potential who desire pregnancy that NSAIDs, including celecoxib capsules, may be associated with a reversible delay in ovulation [see Use in Specific Populations (8.3)].

Fetal Toxicity
Inform pregnant women to avoid use of celecoxib capsules and other NSAIDs starting at 30 weeks of gestation because of the risk of the premature closing of the fetal ductus arteriosus [see Warnings and Precautions (5.10) and Use in Specific Populations (8.1)].

Avoid Concomitant Use of NSAIDs
Inform patients that the concomitant use of celecoxib capsules with other NSAIDs or salicylates (e.g., diflunisal, salsalate) is not recommended due to the increased risk of gastrointestinal toxicity, and little or no increase in efficacy [see Warnings and Precautions (5.2) and Drug Interactions (7)]. Alert patients that NSAIDs may be present in “over the counter” medications for treatment of colds, fever, or insomnia.

Use of NSAIDS and Low-Dose Aspirin
Inform patients not to use low-dose aspirin concomitantly with celecoxib capsules until they talk to their healthcare provider [see Drug Interactions (7)].

Manufactured for :
Macleods Pharma USA, Inc.
Plainsboro, NJ 08536

Manufactured by :
Macleods Pharmaceuticals Ltd.
Baddi, Himachal Pradesh, INDIA

Revision Date: October 2018